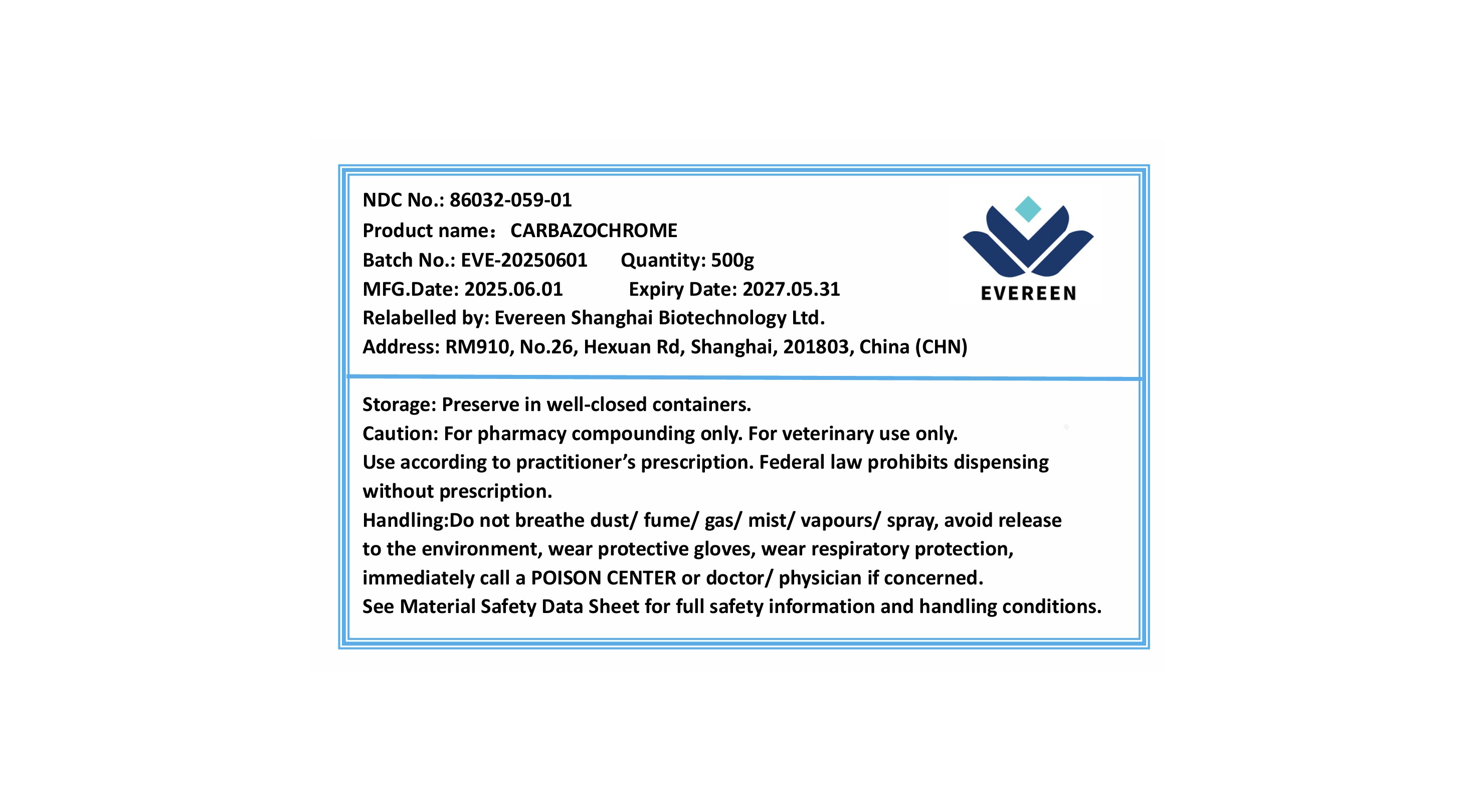 DRUG LABEL: Carbazochrome
NDC: 86032-059 | Form: POWDER
Manufacturer: Evereen Shanghai Biotechnology Ltd.
Category: other | Type: BULK INGREDIENT - ANIMAL DRUG
Date: 20250911

ACTIVE INGREDIENTS: CARBAZOCHROME 1 g/1 g

Carbazochrome